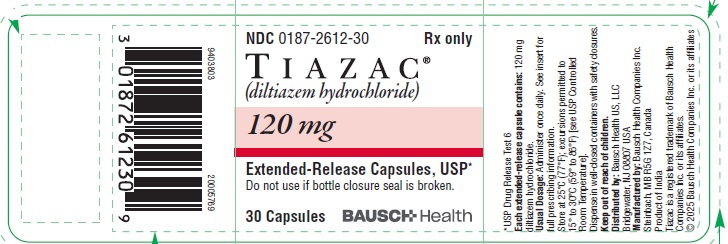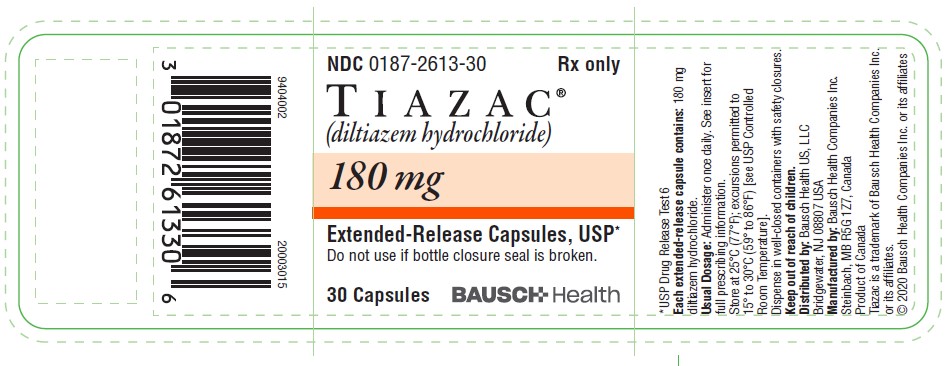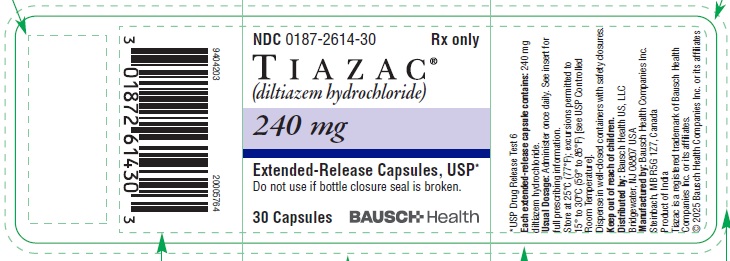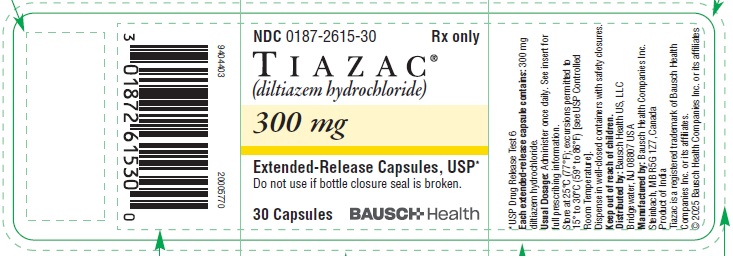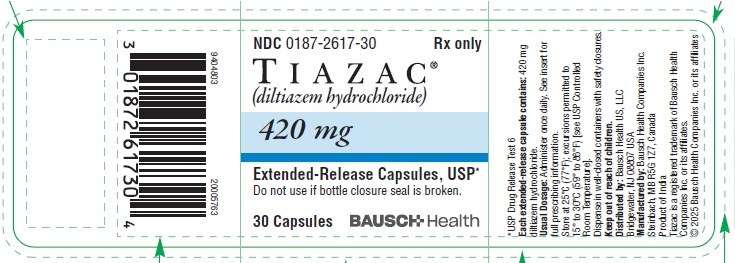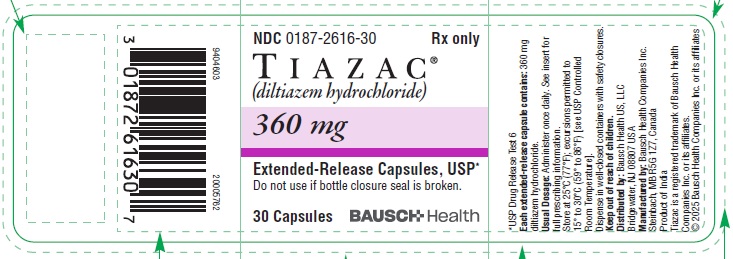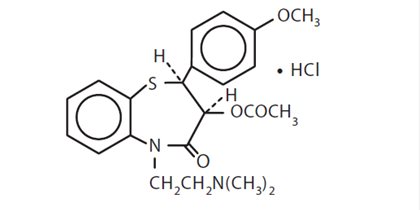 DRUG LABEL: TIAZAC
NDC: 0187-2612 | Form: CAPSULE, EXTENDED RELEASE
Manufacturer: Bausch Health US, LLC
Category: prescription | Type: HUMAN PRESCRIPTION DRUG LABEL
Date: 20251114

ACTIVE INGREDIENTS: DILTIAZEM HYDROCHLORIDE 120 mg/1 1
INACTIVE INGREDIENTS: FERROSOFERRIC OXIDE; D&C RED NO. 28; ETHYL ACRYLATE AND METHYL METHACRYLATE COPOLYMER (2:1; 750000 MW); FD&C BLUE NO. 1; FD&C GREEN NO. 3; FD&C RED NO. 40; GELATIN, UNSPECIFIED; HYPROMELLOSE, UNSPECIFIED; MAGNESIUM STEARATE; MICROCRYSTALLINE CELLULOSE; POLYSORBATE 80; POVIDONE, UNSPECIFIED; SUCROSE STEARATE; TALC; TITANIUM DIOXIDE

Tiazac®
(diltiazem hydrochloride)
Extended-Release Capsules, USP

DESCRIPTION

Tiazac® (diltiazem hydrochloride) is a calcium ion cellular influx inhibitor (slow channel blocker). Chemically, diltiazem hydrochloride is 1,5-Benzothiazepin-4(5H)-one, 3-(acetyloxy)-5-[2-(dimethylamino)ethyl]-2, 3-dihydro-2-(4-methoxyphenyl)-, monohydrochloride, (+)-cis-. The chemical structure is:

Diltiazem hydrochloride is a white to off-white crystalline powder with a bitter taste. It is soluble in water, methanol and chloroform and has a molecular weight of 450.98. Tiazac capsules contain diltiazem hydrochloride in extended-release beads at doses of 120, 180, 240, 300, 360 and 420 mg.

Tiazac also contains: black iron oxide, D&C Red No. 28, ethyl acrylate and methyl methacrylate copolymer dispersion, FD&C Blue No. 1, FD&C Green No. 3, FD&C Red No. 40, gelatin, hypromellose, magnesium stearate, microcrystalline cellulose, polysorbate, povidone, simethicone, sucrose stearate, talc, and titanium dioxide.

USP Drug Release Test 6

For oral administration.

CLINICAL PHARMACOLOGY

The therapeutic effects of diltiazem hydrochloride are believed to be related to its ability to inhibit the cellular influx of calcium ions during membrane depolarization of cardiac and vascular smooth muscle.

Mechanisms of Action

Hypertension: Diltiazem produces its antihypertensive effect primarily by relaxation of vascular smooth muscle and the resultant decrease in peripheral vascular resistance. The magnitude of blood pressure reduction is related to the degree of hypertension: thus hypertensive individuals experience an antihypertensive effect, whereas there is only a modest fall in blood pressure in normotensives.

Angina: Diltiazem hydrochloride has been shown to produce increases in exercise tolerance, probably due to its ability to reduce myocardial oxygen demand. This is accomplished via reductions in heart rate and systemic blood pressure at submaximal and maximal workloads.

Diltiazem has been shown to be a potent dilator of coronary arteries, both epicardial and subendocardial. Spontaneous and ergonovine-induced coronary artery spasms are inhibited by diltiazem.

In animal models, diltiazem interferes with the slow inward (depolarizing) current in excitable tissue. It causes excitation-contraction uncoupling in various myocardial tissues without changes in the configuration of the action potential. Diltiazem produces relaxation of the coronary vascular smooth muscle and dilation of both large and small coronary vascular smooth muscle and dilation of both large and small coronary arteries at drug levels which cause little or no negative inotropic effect. The resultant increases in coronary blood flow (epicardial and subendocardial) occur in ischemic and nonischemic models and are accompanied by dose-dependent decreases in systemic blood pressure and decreases in peripheral resistance.

Hemodynamic and Electrophysiologic Effects

Like other calcium channel antagonists, diltiazem decreases sinoatrial and atrioventricular conduction in isolated tissues and has a negative inotropic effect in isolated preparations. In the intact animal, prolongation of the AH interval can be seen at higher doses.

In man, diltiazem prevents spontaneous and ergonovine-provoked coronary artery spasm. It causes a decrease in peripheral vascular resistance and a modest fall in blood pressure in normotensive individuals and, in exercise tolerance studies in patients with ischemic heart disease, reduces the heart rate-blood pressure product for any given workload. Studies to date, primarily in patients with good ventricular function, have not revealed evidence of a negative inotropic effect; cardiac output, ejection fraction, and left ventricular end-diastolic pressure have not been affected. Such data have no predictive value with respect to effects in patients with poor ventricular function, and increased heart failure has been reported in patients with preexisting impairment of ventricular function. There are as yet few data on the interaction of diltiazem and beta-blockers in patients with poor ventricular function. Resting heart rate is usually slightly reduced by diltiazem.

Tiazac produces antihypertensive effects both in the supine and standing positions. Postural hypotension is infrequently noted upon suddenly assuming an upright position. No reflex tachycardia is associated with the chronic antihypertensive effects.

Diltiazem hydrochloride decreases vascular resistance, increases cardiac output (by increasing stroke volume), and produces a slight decrease or no change in heart rate. During dynamic exercise, increases in diastolic pressure are inhibited while maximum achievable systolic pressure is usually reduced. Chronic therapy with diltiazem hydrochloride produces no change or an increase in plasma catecholamines. No increased activity of the renin-angiotensin-aldosterone axis has been observed. Diltiazem hydrochloride reduces the renal and peripheral effects of angiotensin II. Hypertensive animal models respond to diltiazem with reductions in blood pressure and increased urinary output and natriuresis without a change in urinary sodium/potassium ratio. In man, transient natriuresis and kaliuresis have been reported, but only in high intravenous doses of 0.5 mg/kg of body weight.

Diltiazem-associated prolongation of the AH interval is not more pronounced in patients with first-degree heart block. In patients with sick sinus syndrome, diltiazem significantly prolongs sinus cycle length (up to 50% in some cases). Intravenous diltiazem in doses of 20 mg prolongs AH conduction time and AV node functional and effective refractory periods by approximately 20%.

In two short-term, double-blind, placebo-controlled studies in 256 hypertensive patients with doses up to 540 mg/day, Tiazac showed a clinically unimportant but statistically significant, dose-related increase in PR interval (0.008 seconds). There were no instances of greater than first-degree AV block in any of the clinical trials (see WARNINGS).

Pharmacodynamics

Hypertension: In short-term, double-blind, placebo-controlled clinical trials Tiazac demonstrated a dose-related antihypertensive response among patients with mild to moderate hypertension. In one parallel-group study of 198 patients Tiazac was given for four weeks. The changes in diastolic blood pressure measured at trough (24 hours after the dose) for placebo, 90 mg, 180 mg, 360 mg and 540 mg were -5.4, -6.3, -6.2, -8.2, and -11.8 mm Hg, respectively. Supine diastolic blood pressure as well as standing diastolic and systolic blood pressures also showed statistically significant linear dose response effects.

In another clinical trial that followed a dose-escalation design, Tiazac also reduced blood pressure in a linear dose-related manner. Supine diastolic blood pressure measured following two-week intervals of treatment was reduced by -3.7 mm Hg with 120 mg/day versus -2.0 mm Hg with placebo, by -7.6 mm Hg after escalation to 240 mg/day versus -2.3 mm Hg with placebo, by -8.1 mm Hg after escalation to 360 mg/day versus -0.9 mm Hg with placebo, and by -10.8 mm Hg after escalation to 480/540 mg/day versus -2.2 mm Hg with placebo.

Angina: In a double-blind, parallel-group, placebo-controlled trial (approximately 50 patients/group, in patients with chronic stable angina), Tiazac at doses of 120 to 540 mg/day increased exercise tolerance time. At trough, 24 hours after dosing, exercise tolerance times using a Bruce exercise protocol, increased by 14, 26, 41, 33 and 32 seconds over baseline for placebo and the 120 mg, 240 mg, 360 mg, and 540 mg treated patient groups, respectively. At peak, 8 hours after dosing, exercise tolerance times relative to baseline were statistically significantly increased by 13, 38, 64, 55 and 42 seconds for placebo and 120 mg, 240 mg, 360 mg, and 540 mg Tiazac treated patients, respectively. Compared to baseline, Tiazac treated patients experienced statistically significant reductions in anginal attacks and decreased nitroglycerin requirements when compared to placebo treated patients.

Pharmacokinetics and Metabolism

Diltiazem is well absorbed from the gastrointestinal tract but undergoes substantial hepatic first-pass effect. The absolute bioavailability of an oral dose of an immediate-release formulation (compared to intravenous administration) is approximately 40%. Only 2% to 4% of unchanged diltiazem appears in the urine. The plasma elimination half-life of diltiazem is approximately 3.0 to 4.5 hours. Drugs which induce or inhibit hepatic microsomal enzymes may alter diltiazem disposition. Therapeutic blood levels of diltiazem appear to be in the range of 40 to 200 ng/mL. There is a departure from linearity when dose strengths are increased; the half-life is slightly increased with dose.

The two primary metabolites of diltiazem are desacetyldiltiazem and desmethyldiltiazem. The desacetyl metabolite is approximately 25% to 50% as potent a coronary vasodilator as diltiazem and is present in plasma at concentrations of 10% to 20% of parent diltiazem. However, recent studies employing sensitive and specific analytical methods have confirmed the existence of several sequential metabolic pathways of diltiazem. As many as nine diltiazem metabolites have been identified in the urine of humans. Total radioactivity measurements following single intravenous dose administration in healthy volunteers suggest the presence of other unidentified metabolites. These metabolites are more slowly excreted (with a half-life of total radioactivity of approximately 20 hours) and attain concentrations in excess of diltiazem.

In vitro binding studies show diltiazem hydrochloride is 70% to 80% bound to plasma proteins. Competitive in vitro ligand binding studies have also shown diltiazem hydrochloride binding is not altered by therapeutic concentrations of digoxin, hydrochlorothiazide, phenylbutazone, propranolol, salicylic acid, or warfarin. A study that compared patients with normal hepatic function to patients with cirrhosis who received immediate-release diltiazem found an increase in diltiazem elimination half-life and a 69% increase in bioavailability in the hepatically impaired patients. Patients with severely impaired renal function (creatinine clearance <50 mL/min) who received immediate-release diltiazem had modestly increased diltiazem concentrations compared to patients with normal renal function.

Tiazac Capsules: When compared to a regimen of immediate-release tablets at steady-state, approximately 93% of drug is absorbed from the Tiazac formulation. When Tiazac was coadministered with a high fat content breakfast, the extent of diltiazem absorption was not affected; Tmax, however, occurred slightly earlier. The apparent elimination half-life after single or multiple dosing is 4 to 9.5 hours (mean 6.5 hours).

Tiazac demonstrates non-linear pharmacokinetics. As the daily dose of Tiazac capsules was increased from 120 to 540 mg, there was a more than proportional increase in diltiazem plasma concentrations as evidenced by an increase of AUC, Cmax and Cmin of 6.8, 6 and 8.6 times, respectively, for a 4.5 times increase in dose.

INDICATIONS AND USAGE

Hypertension

Tiazac is indicated for the treatment of hypertension. It may be used alone or in combination with other antihypertensive medications.

Chronic Stable Angina

Tiazac is indicated for the treatment of chronic stable angina.

CONTRAINDICATIONS

Diltiazem is contraindicated in:

- Patients with sick sinus syndrome except in the presence of a functioning ventricular pacemaker
- Patients with second- or third-degree AV block except in the presence of a functioning ventricular pacemaker
- Patients with severe hypotension (less than 90 mm Hg systolic)
- Patients who have demonstrated hypersensitivity to the drug
- Patients with acute myocardial infarction and pulmonary congestion documented by x-ray on admission.

WARNINGS

1. Cardiac Conduction: Diltiazem hydrochloride prolongs AV node refractory periods without significantly prolonging sinus node recovery time, except in patients with sick sinus syndrome. This effect may rarely result in abnormally slow heart rates (particularly in patients with sick sinus syndrome) or second- or third-degree AV block (13 of 3007 patients or 0.43%). Concomitant use of diltiazem with beta-blockers or digitalis may result in additive effects on cardiac conduction. A patient with Prinzmetal’s angina developed periods of asystole (2 to 5 seconds) after a single dose of 60 mg of diltiazem.

2. Congestive Heart Failure: Although diltiazem has a negative inotropic effect in isolated animal tissue preparations, hemodynamic studies in humans with normal ventricular function have not shown a reduction in cardiac index nor consistent negative effects on contractility (dP/dt). An acute study of oral diltiazem in patients with impaired ventricular function (ejection fraction 24% ± 6%) showed improvement in indices of ventricular function without significant decrease in contractile function (dP/dt). Worsening of congestive heart failure has been reported in patients with preexisting impairment of ventricular function. Experience with the use of diltiazem hydrochloride in combination with beta-blockers in patients with impaired ventricular function is limited. Caution should be exercised when using this combination.

3. Hypotension: Decreases in blood pressure associated with diltiazem hydrochloride therapy may occasionally result in symptomatic hypotension.

4. Acute Hepatic Injury: Mild elevations of transaminases with and without concomitant elevation in alkaline phosphatase and bilirubin have been observed in clinical studies. Such elevations were usually transient and frequently resolved even with continued diltiazem treatment. In rare instances, significant elevations in enzymes such as alkaline phosphatase, LDH, SGOT, and SGPT, and other phenomena consistent with acute hepatic injury have been noted. These reactions tended to occur early after therapy initiation (1 to 8 weeks) and have been reversible upon discontinuation of drug therapy. The relationship to diltiazem hydrochloride is uncertain in some cases but probable in some (see PRECAUTIONS).

PRECAUTIONS

General

Diltiazem hydrochloride is extensively metabolized by the liver and excreted by the kidneys and in bile. As with any drug given over prolonged periods, laboratory parameters of renal and hepatic function should be monitored at regular intervals. The drug should be used with caution in patients with impaired renal or hepatic function. In subacute and chronic dog and rat studies designed to produce toxicity, high doses of diltiazem were associated with hepatic damage. In special subacute hepatic studies, oral doses of 125 mg/kg and higher in rats were associated with histological changes in the liver which were reversible when the drug was discontinued. In dogs, doses of 20 mg/kg were also associated with hepatic changes; however, these changes were reversible with continued dosing.

Dermatological events (see ADVERSE REACTIONS) may be transient and may disappear despite continued use of diltiazem hydrochloride. However, skin eruptions progressing to erythema multiforme and/or exfoliative dermatitis have also been infrequently reported. Should a dermatologic reaction persist, the drug should be discontinued.

Drug Interactions

Due to the potential for additive effects, caution and careful titration are warranted in patients receiving diltiazem hydrochloride concomitantly with other agents known to affect cardiac contractility and/or conduction (see WARNINGS). Pharmacologic studies indicate that there may be additive effects in prolonging AV conduction when using beta-blockers or digitalis concomitantly with Tiazac (see WARNINGS). Diltiazem is both a substrate and an inhibitor of the Pg-p and cytochrome P450 3A4 enzyme system which may affect exposure to diltiazem and concomitant drugs metabolized by those pathways. Patients with renal and/or hepatic impairment may be particularly at risk of exposure changes.

Anesthetics: The depression of cardiac contractility, conductivity, and automaticity as well as the vascular dilation associated with anesthetics may be potentiated by calcium channel blockers. When used concomitantly, anesthetics and calcium channel blockers should be titrated carefully.

Benzodiazepines: Studies showed that diltiazem increased the AUC of midazolam and triazolam by 3- to 4-fold and the Cmax by 2-fold, compared to placebo. The elimination half-life of midazolam and triazolam also increased (1.5- to 2.5-fold) during coadministration with diltiazem. These pharmacokinetic effects seen during diltiazem coadministration can result in increased clinical effects (e.g., prolonged sedation) of both midazolam and triazolam.

Beta-blockers: Controlled and uncontrolled domestic studies suggest that concomitant use of diltiazem hydrochloride and beta-blockers is usually well tolerated, but available data are not sufficient to predict the effects of concomitant treatment in patients with left ventricular dysfunction or cardiac conduction abnormalities. Administration of diltiazem hydrochloride concomitantly with propranolol in five normal volunteers resulted in increased propranolol levels in all subjects and bioavailability of propranolol was increased approximately 50%. In vitro, propranolol appears to be displaced from its binding sites by diltiazem. If combination therapy is initiated or withdrawn in conjunction with propranolol, an adjustment in the propranolol dose may be warranted (see WARNINGS).

Buspirone: In nine healthy subjects, diltiazem significantly increased the mean buspirone AUC 5.5-fold and Cmax 4.1-fold compared to placebo. The T½ and Tmax of buspirone were not significantly affected by diltiazem. Enhanced effects and increased toxicity of buspirone may be possible during concomitant administration with diltiazem. Subsequent dose adjustments may be necessary during coadministration, and should be based on clinical assessment.

Carbamazepine: Concomitant administration of diltiazem with carbamazepine has been reported to result in elevated serum levels of carbamazepine (40% to 72% increase), resulting in toxicity in some cases. Patients receiving these drugs concurrently should be monitored for a potential drug interaction.

Cimetidine: A study in six healthy volunteers has shown a significant increase in peak diltiazem plasma levels (58%) and AUC (53%) after a 1-week course of cimetidine 1200 mg/day and a single dose of diltiazem 60 mg. Ranitidine produced smaller, nonsignificant increases. The effect may be mediated by cimetidine’s known inhibition of hepatic cytochrome P450, the enzyme system responsible for the first-pass metabolism of diltiazem. Patients currently receiving diltiazem therapy should be carefully monitored for a change in pharmacological effect when initiating and discontinuing therapy with cimetidine. An adjustment in the diltiazem dose may be warranted.

Clonidine: Sinus bradycardia resulting in hospitalization and pacemaker insertion has been reported in association with the use of clonidine concurrently with diltiazem. Monitor heart rate in patients receiving concomitant diltiazem and clonidine.

Cyclosporine: A pharmacokinetic interaction between diltiazem and cyclosporine has been observed during studies involving renal and cardiac transplant patients. In renal and cardiac transplant recipients, a reduction of cyclosporine dose ranging from 15% to 48% was necessary to maintain cyclosporine trough concentrations similar to those seen prior to the addition of diltiazem. If these agents are to be administered concurrently, cyclosporine concentrations should be monitored, especially when diltiazem therapy is initiated, adjusted, or discontinued.

The effect of cyclosporine on diltiazem plasma concentrations has not been evaluated.

Digitalis: Administration of diltiazem hydrochloride with digoxin in 24 healthy male subjects increased plasma digoxin concentrations approximately 20%. Another investigator found no increase in digoxin levels in 12 patients with coronary artery disease. Since there have been conflicting results regarding the effect of digoxin levels, it is recommended that digoxin levels be monitored when initiating, adjusting, and discontinuing diltiazem hydrochloride therapy to avoid possible over- or under-digitalization (see WARNINGS).

Ivabradine: Concurrent use of diltiazem increases exposure to ivabradine and may exacerbate bradycardia and conduction disturbances. Avoid concomitant use of ivabradine and diltiazem.

Quinidine: Diltiazem significantly increases the AUC(0→∞) of quinidine by 51%, T½ by 36%, and decreases its CLoral by 33%. Monitoring for quinidine adverse effects may be warranted and the dose adjusted accordingly.

Rifampin: Coadministration of rifampin with diltiazem lowered the diltiazem plasma concentrations to undetectable levels. Coadministration of diltiazem with rifampin or any known CYP3A4 inducer should be avoided when possible, and alternative therapy considered.

Statins: Diltiazem is an inhibitor of CYP3A4 and has been shown to increase significantly the AUC of some statins. The risk of myopathy and rhabdomyolysis with statins metabolized by CYP3A4 is increased with concomitant use of diltiazem. When possible, use a non-CYP3A4-metabolized statin with diltiazem. Otherwise, reduce the dose for both diltiazem and the statin and monitor for signs and symptoms of muscle toxicity.

In a healthy volunteer cross-over study (N=10), coadministration of a single 20 mg dose of simvastatin at the end of a 14-day regimen with 120 mg BID diltiazem SR resulted in a 5-fold increase in mean simvastatin AUC versus simvastatin alone. Subjects with increased average steady-state exposures of diltiazem showed a greater increase in simvastatin exposure. If coadministration of simvastatin with diltiazem is required, limit the daily doses of simvastatin to 10 mg and diltiazem to 240 mg.

In a ten-subject randomized, open-label, 4-way cross-over study, coadministration of diltiazem (120 mg BID diltiazem SR for 2 weeks) with a single 20 mg dose of lovastatin resulted in 3- to 4-fold increase in mean lovastatin AUC and Cmax versus lovastatin alone. In the same study, there was no significant change in 20 mg single dose pravastatin AUC and Cmax during diltiazem coadministration. Diltiazem plasma levels were not significantly affected by lovastatin or pravastatin.

Carcinogenesis, Mutagenesis, Impairment of Fertility

A 24-month study in rats at oral dosage levels of up to 100 mg/kg/day and a 21-month study in mice at oral dosage levels of up to 30 mg/kg/day showed no evidence of carcinogenicity. There was also no mutagenic response in vitro or in vivo in mammalian cell assays or in vitro in bacteria. No evidence of impaired fertility was observed in a study performed in male and female rats at oral dosages of up to 100 mg/kg/day.

Pregnancy

Reproduction studies have been conducted in mice, rats, and rabbits. Administration of doses ranging from 4 to 6 times (depending on species) the upper limit of the optimum dosage range in clinical trials (480 mg/day or 8 mg/kg/day for a 60-kg patient) resulted in embryo and fetal lethality. These studies revealed, in one species or another, a propensity to cause abnormalities of the skeleton, heart, retina, and tongue. Also observed were reductions in early individual pup weights and pup survival, prolonged delivery and increased incidence of stillbirths. There are no well-controlled studies in pregnant women; therefore, use diltiazem hydrochloride in pregnant women only if the potential benefit justifies the potential risk to the fetus.

Nursing Mothers

Diltiazem is excreted in human milk. One report suggests that concentrations in breast milk may approximate serum levels. If use of Tiazac is deemed essential, an alternative method of infant feeding should be instituted.

Pediatric Use

Safety and effectiveness in children have not been established.

Geriatric Use

Clinical studies of diltiazem did not include sufficient numbers of subjects aged 65 and over to determine whether they respond differently from younger subjects. Other reported clinical experience has not identified differences in responses between the elderly and younger patients. In general, dose selection for an elderly patient should be cautious, usually starting at the low end of the dosing range, reflecting the greater frequency of decreased hepatic, renal, or cardiac function, and of concomitant disease or other drug therapy.

ADVERSE REACTIONS

Serious adverse reactions have been rare in studies with Tiazac, as well as with other diltiazem formulations. It should be recognized that patients with impaired ventricular function and cardiac conduction abnormalities have usually been excluded from these studies. A total of 256 hypertensives were treated for between 4 and 8 weeks; a total of 207 patients with chronic stable angina were treated for 3 weeks with doses of Tiazac ranging from 120 to 540 mg once daily. Two patients experienced first-degree AV block at the 540 mg dose. The following table presents the most common adverse reactions, whether or not drug-related, reported in placebo-controlled trials in patients receiving Tiazac up to 360 mg and up to 540 mg with rates in placebo patients shown for comparison.

MOST COMMON ADVERSE EVENTS IN DOUBLE-BLIND PLACEBO-CONTROLLED HYPERTENSION TRIALS [Adverse events occurring in treated patients at 2% or more than placebo-treated patients.]
 | Placebo | Tiazac
Adverse Events (COSTART Term) | n=57 # pts (%) | Up to 360 mg n=149 # pts (%) | 480 - 540 mg n=48 # pts (%)
edema, peripheral | 1 (2) | 8 (5) | 7 (15)
dizziness | 4 (7) | 6 (4) | 2 (4)
vasodilation | 1 (2) | 5 (3) | 1 (2)
dyspepsia | 0 (0) | 7 (5) | 0 (0)
pharyngitis | 2 (4) | 3 (2) | 3 (6)
rash | 0 (0) | 3 (2) | 0 (0)
infection | 2 (4) | 2 (1) | 3 (6)
diarrhea | 0 (0) | 2 (1) | 1 (2)
palpitations | 0 (0) | 2 (1) | 1 (2)
nervousness | 0 (0) | 3 (2) | 0 (0)

MOST COMMON ADVERSE EVENTS IN DOUBLE-BLIND PLACEBO-CONTROLLED ANGINA TRIALS [Adverse events occurring in treated patients at 2% or more than placebo-treated patients.]
 | Placebo | Tiazac
Adverse Events (COSTART Term) | n=50 # pts (%) | Up to 360 mg n=158 # pts (%) | 540 mg n=49 # pts (%)
headache | 1 (2) | 13 (8) | 4 (8)
edema, peripheral | 1 (2) | 3 (2) | 5 (10)
pain | 1 (2) | 10 (6) | 3 (6)
dizziness | 0 (0) | 5 (3) | 5 (10)
asthenia | 0 (0) | 1 (1) | 2 (4)
dyspepsia | 0 (0) | 2 (1) | 3 (6)
dyspnea | 0 (0) | 1 (1) | 3 (6)
bronchitis | 0 (0) | 1 (1) | 2 (4)
AV block | 0 (0) | 0 (0) | 2 (4)
infection | 0 (0) | 2 (1) | 1 (2)
flu syndrome | 0 (0) | 0 (0) | 1 (2)
cough increase | 0 (0) | 2 (1) | 1 (2)
extrasystoles | 0 (0) | 0 (0) | 1 (2)
gout | 0 (0) | 2 (1) | 1 (2)
myalgia | 0 (0) | 0 (0) | 1 (2)
impotence | 0 (0) | 0 (0) | 1 (2)
conjunctivitis | 0 (0) | 0 (0) | 1 (2)
rash | 0 (0) | 2 (1) | 1 (2)
abdominal enlargement | 0 (0) | 0 (0) | 1 (2)

In addition, the following events have been reported infrequently (less than 2%) in clinical trials with other diltiazem products:

Cardiovascular: Angina, arrhythmia, AV block (second- or third-degree), bundle branch block, congestive heart failure, ECG abnormalities, hypotension, palpitations, syncope, tachycardia, ventricular extrasystoles.

Nervous System: Abnormal dreams, amnesia, depression, gait abnormality, hallucinations, insomnia, nervousness, paresthesia, personality change, somnolence, tinnitus, tremor.

Gastrointestinal: Anorexia, constipation, diarrhea, dry mouth, dysgeusia, mild elevations of SGOT, SGPT, LDH, and alkaline phosphatase (see WARNINGS, Acute Hepatic Injury), nausea, thirst, vomiting, weight increase.

Dermatological: Petechiae, photosensitivity, pruritus.

Other: Albuminuria, allergic reaction, amblyopia, asthenia, CPK increase, crystalluria, dyspnea, edema, epistaxis, eye irritation, headache, hyperglycemia, hyperuricemia, impotence, muscle cramps, nasal congestion, neck rigidity, nocturia, osteoarticular pain, pain, polyuria, rhinitis, sexual difficulties, gynecomastia.

In addition, the following postmarketing events have been reported infrequently in patients receiving diltiazem hydrochloride: acute generalized exanthematous pustulosis, alopecia, erythema multiforme, exfoliative dermatitis, Stevens-Johnson syndrome, toxic epidermal necrolysis, extrapyramidal symptoms, gingival hyperplasia, hemolytic anemia, increased bleeding time, photosensitivity (including lichenoid keratosis and hyperpigmentation at sun-exposed skin areas), leukopenia, purpura, retinopathy, and thrombocytopenia. In addition, events such as myocardial infarction have been observed which are not readily distinguishable from the natural history of the disease in these patients. A number of well-documented cases of generalized rash, characterized as leukocytoclastic vasculitis, have been reported. However, a definitive cause and effect relationship between these events and diltiazem hydrochloride therapy is yet to be established.

To report SUSPECTED ADVERSE REACTIONS, contact Bausch Health US, LLC at 1-800-321-4576 or FDA at 1-800-FDA-1088 or www.fda.gov/medwatch.

OVERDOSAGE

The oral LD50S in mice and rats range from 415 to 740 mg/kg and from 560 to 810 mg/kg, respectively. The intravenous LD50S in these species were 60 and 38 mg/kg, respectively. The oral LD50 in dogs is considered to be in excess of 50 mg/kg, while lethality was seen in monkeys at 360 mg/kg.

The toxic dose in man is not known. Due to extensive metabolism, blood levels after a standard dose of diltiazem can vary over tenfold, limiting the usefulness of blood levels in overdose cases. There have been 29 reports of diltiazem overdose in doses ranging from less than 1 g to 10.8 g. Sixteen of these reports involved multiple drug ingestions. Twenty-two reports indicated patients had recovered from diltiazem overdose ranging from less than 1 g to 10.8 g. There were seven reports with a fatal outcome; although the amount of diltiazem ingested was unknown, multiple drug ingestions were confirmed in six of the seven reports.

Events observed following diltiazem overdose included bradycardia, hypotension, heart block, and cardiac failure. Most reports of overdose described some supportive medical measure and/or drug treatment. Bradycardia frequently responded favorably to atropine as did heart block, although cardiac pacing was also frequently utilized to treat heart block. Fluids and vasopressors were used to maintain blood pressure, and in cases of cardiac failure, inotropic agents were administered. In addition, some patients received treatment with ventilatory support, activated charcoal, and/or intravenous calcium. Evidence of the effectiveness of intravenous calcium administration to reverse the pharmacological effects of diltiazem overdose was conflicting.

In the event of overdose or exaggerated response, appropriate supportive measures should be employed in addition to gastrointestinal decontamination. Diltiazem does not appear to be removed by peritoneal or hemodialysis. Based on the known pharmacological effects of diltiazem and/or reported clinical experiences, the following measures may be considered:

Bradycardia: Administer atropine (0.60 to 1.0 mg). If there is no response to vagal blockage, administer isoproterenol cautiously.

High-Degree AV Block: Treat as for bradycardia above. Fixed high-degree AV block should be treated with cardiac pacing.

Cardiac Failure: Administer inotropic agents (isoproterenol, dopamine, or dobutamine) and diuretics.

Hypotension: Vasopressors (e.g., dopamine or norepinephrine). Actual treatment and dosage should depend on the severity of the clinical situation and the judgment and experience of the treating physician.

In a few reported cases, overdose with calcium channel blockers has been associated with hypotension and bradycardia, initially refractory to atropine but becoming more responsive to this treatment when the patients received large doses (close to 1 gram/hour for more than 24 hours) of calcium chloride.

Due to extensive metabolism, plasma concentrations after a standard dose of diltiazem can vary over tenfold, which significantly limits their value in evaluation cases of overdosage.

Charcoal hemoperfusion has been used successfully as an adjunct therapy to hasten drug elimination. Overdoses with as much as 10.8 g of oral diltiazem have been successfully treated using appropriate supportive care.

DOSAGE AND ADMINISTRATION

Hypertension: Dosage needs to be adjusted by titration to individual patient needs. When used as monotherapy, usual starting doses are 120 to 240 mg once daily. Maximum antihypertensive effect is usually observed by 14 days of chronic therapy; therefore, dosage adjustments should be scheduled accordingly. The usual dosage range studied in clinical trials was 120 to 540 mg once daily. Current clinical experience with 540 mg dose is limited; however, the dose may be increased to 540 mg once daily.

Angina: Dosages for the treatment of angina should be adjusted to each patient’s needs, starting with a dose of 120 mg to 180 mg once daily. Individual patients may respond to higher doses of up to 540 mg once daily. When necessary, titration should be carried out over 7 to 14 days.

Concomitant Use with Other Cardiovascular Agents:

1. Sublingual Nitroglycerin (NTG): May be taken as required to abort acute anginal attacks during diltiazem hydrochloride therapy.

2. Prophylactic Nitrate Therapy: Diltiazem hydrochloride may be safely coadministered with short- and long-acting nitrates.

3. Beta-blockers: (see WARNINGS and PRECAUTIONS).

4. Antihypertensives: Diltiazem hydrochloride has an additive antihypertensive effect when used with other antihypertensive agents. Therefore, the dosage of diltiazem hydrochloride or the concomitant antihypertensives may need to be adjusted when adding one to the other.

Hypertensive or anginal patients who are treated with other formulations of diltiazem can safely be switched to Tiazac capsules at the nearest equivalent total daily dose. Subsequent titration to higher or lower doses may, however, be necessary and should be initiated as clinically indicated.

Sprinkling the Capsule Contents on Food:

Tiazac (diltiazem hydrochloride) Extended-Release Capsules may also be administered by carefully opening the capsule and sprinkling the capsule contents on a spoonful of applesauce. The applesauce should be swallowed immediately without chewing and followed with a glass of cool water to ensure complete swallowing of the capsule contents. The applesauce should not be hot, and it should be soft enough to be swallowed without chewing. Any capsule contents/applesauce mixture should be used immediately and not stored for future use. Subdividing the contents of a Tiazac (diltiazem hydrochloride) Extended-Release Capsule is not recommended.

HOW SUPPLIED

Tiazac® (diltiazem hydrochloride) Extended-Release Capsules, USP

Strength | Description | Quantity | NDC#
120 mg | #3 lavender/lavender capsule; imprinted: Tiazac 120 | 30; 90 | 0187-2612-30; 0187-2612-90
180 mg | #2 white/blue-green capsule; imprinted: Tiazac 180 | 30; 90 | 0187-2613-30; 0187-2613-90
240 mg | #1 blue-green/lavender capsule; imprinted: Tiazac 240 | 30; 90 | 0187-2614-30; 0187-2614-90
300 mg | #0 white/lavender capsule; imprinted: Tiazac 300 | 30; 90 | 0187-2615-30; 0187-2615-90
360 mg | #0 blue-green/blue-green capsule; imprinted: Tiazac 360 | 30; 90 | 0187-2616-30; 0187-2616-90
420 mg | #00 white/white capsule; imprinted: Tiazac 420 | 30; 90 | 0187-2617-30; 0187-2617-90

STORAGE AND HANDLING

Storage Conditions: Store at 25°C (77°F); excursions permitted to 15° to 30°C (59° to 86°F) [see USP Controlled Room Temperature]. Avoid excessive humidity.

Distributed by:
Bausch Health US, LLC
Bridgewater, NJ 08807 USA

Manufactured by:
Bausch Health Companies Inc.
Steinbach, MB R5G 1Z7, Canada

Tiazac is a registered trademark of Bausch Health Companies Inc. or its affiliates.
© 2025 Bausch Health Companies Inc. or its affiliates

Rev. 04/2025

9405004 20005747

PRINCIPAL DISPLAY PANEL - 120 mg Capsule Bottle Label

NDC 0187-2612-30

Rx only

T I A Z A C®
(diltiazem hydrochloride)

120 mg

Extended-Release Capsules, USP*
Do not use if bottle closure seal is broken.

30 Capsules

BAUSCH Health

PRINCIPAL DISPLAY PANEL - 180 mg Capsule Bottle Label

NDC 0187-2613-30

Rx only

T I A Z A C®
(diltiazem hydrochloride)

180 mg

Extended-Release Capsules, USP*
Do not use if bottle closure seal is broken.

30 Capsules

BAUSCH Health

PRINCIPAL DISPLAY PANEL - 240 mg Capsule Bottle Label

NDC 0187-2614-30

Rx only

T I A Z A C®
(diltiazem hydrochloride)

240 mg

Extended-Release Capsules, USP*
Do not use if bottle closure seal is broken.

30 Capsules

BAUSCH Health

PRINCIPAL DISPLAY PANEL - 300 mg Capsule Bottle Label

NDC 0187-2615-30

Rx only

T I A Z A C®
(diltiazem hydrochloride)

300 mg

Extended-Release Capsules, USP*
Do not use if bottle closure is broken.

30 Capsules

BAUSCH Health

PRINCIPAL DISPLAY PANEL - 360 mg Capsule Bottle Label

NDC 0187-2616-30

Rx only

T I A Z A C®
(diltiazem hydrochloride)

360 mg

Extended-Release Capsules, USP*
Do not use if bottle closure seal is broken.

30 Capsules

BAUSCH Health

PRINCIPAL DISPLAY PANEL - 420 mg Capsule Bottle Label

NDC0187-2617-30

Rx only

T I A Z A C®
(diltiazem hydrochloride)

420 mg

Extended-Release Capsules, USP*
Do not use if bottle closure seal is broken.

30 Capsules

BAUSCH Health